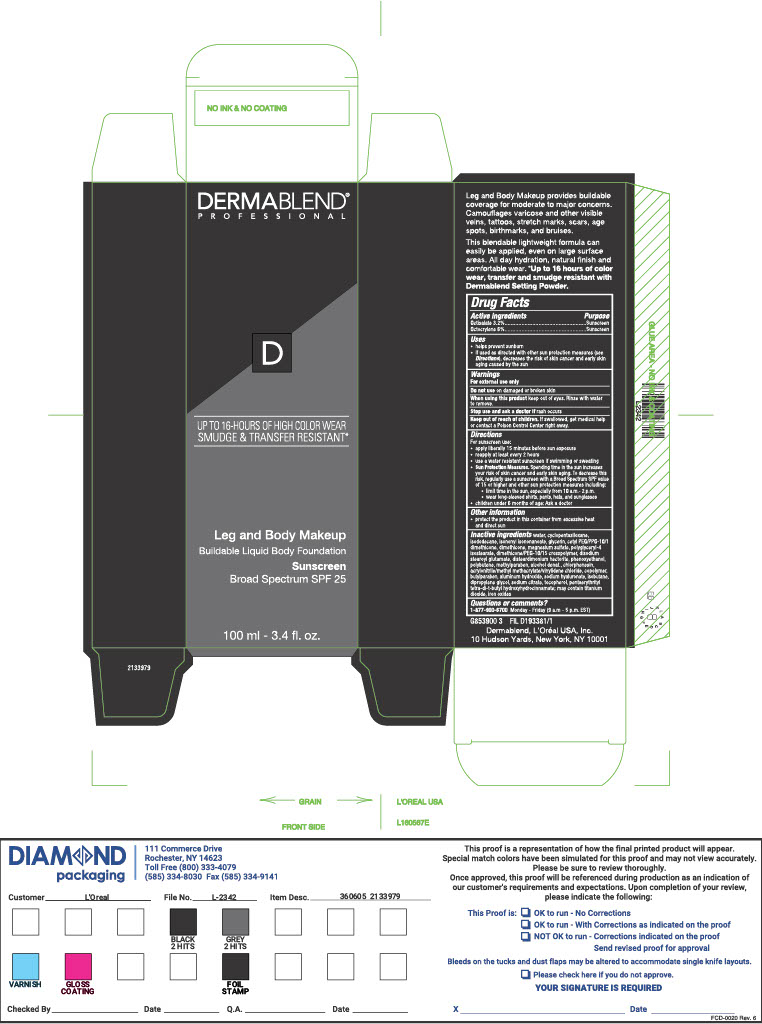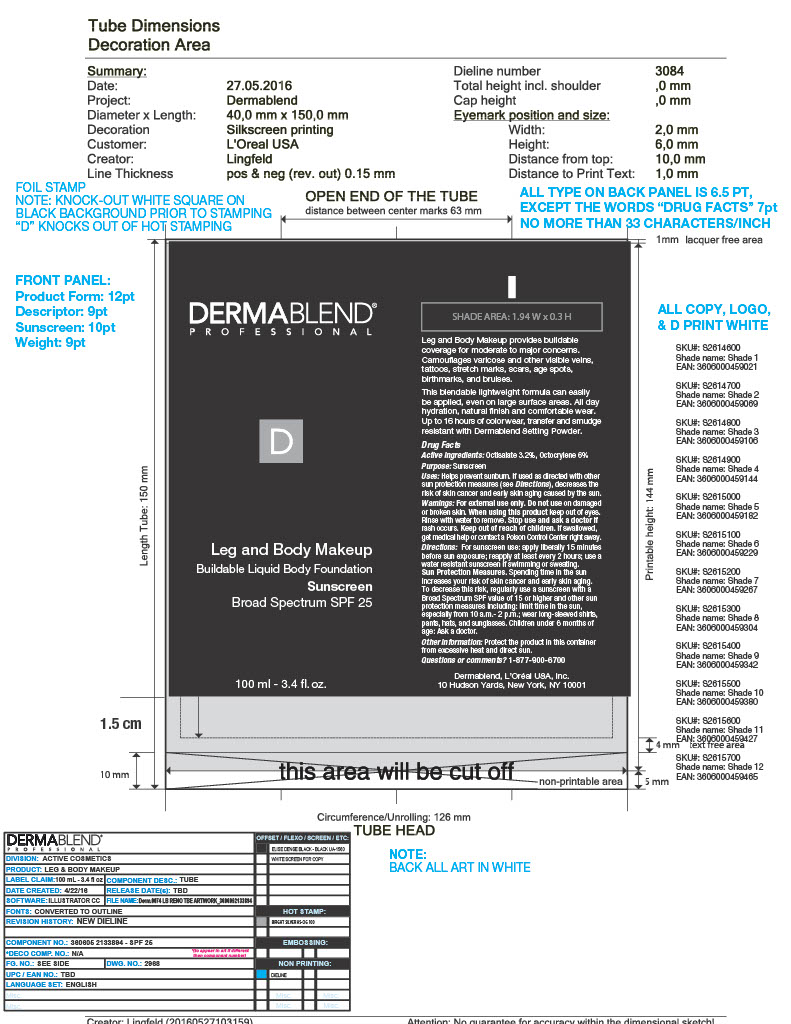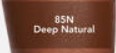 DRUG LABEL: Leg Body Makeup
NDC: 68577-114 | Form: CREAM
Manufacturer: COSMAX USA, CORPORATION
Category: otc | Type: HUMAN OTC DRUG LABEL
Date: 20241225

ACTIVE INGREDIENTS: OCTOCRYLENE 6 mg/100 mg; OCTISALATE 3.2 mg/100 mg
INACTIVE INGREDIENTS: CYCLOMETHICONE 5; GLYCERIN; POLYGLYCERYL-4 ISOSTEARATE; ALUMINUM HYDROXIDE; HYALURONATE SODIUM; ISOBUTANE; DIMETHICONE/PEG-10/15 CROSSPOLYMER; PHENOXYETHANOL; ISONONYL ISONONANOATE; ISODODECANE; CETYL PEG/PPG-10/1 DIMETHICONE (HLB 1.5); TITANIUM DIOXIDE; FERROUS OXIDE; WATER; DIMETHICONE; DISTEARDIMONIUM HECTORITE; BUTYLPARABEN; SODIUM CITRATE; TOCOPHEROL; PENTAERYTHRITOL TETRAKIS(3-(3,5-DI-TERT-BUTYL-4-HYDROXYPHENYL)PROPIONATE); ALCOHOL; DIPROPYLENE GLYCOL; MAGNESIUM SULFATE, UNSPECIFIED FORM; METHYLPARABEN; DISODIUM STEAROYL GLUTAMATE; POLYBUTENE (1400 MW); CHLORPHENESIN; GLATIRAMER ACETATE

DERMABLEND Leg and Body Makeup SPF25- DEEP NATURAL

Active Ingredients

Octisalate 3.2%

Octocrylene 6.2%

Purpose

Sunscreen

USES

- helps prevent sunburn
- if used as directed with other sun protection measures (see Directions), decreases the risk of skin cancer and early skin aging cause by the sun

Warnings

For extenal use only

Do not useon damaged or broken skin

WHEN USING

When using this productkeep out of eyes. Rinse with water to remove.

Stop use and ask a doctor ifrash occurs

Keep out of reach of children.If swallowed, get medical help or contact a Poison Control Center right away.

DIRECTIONS

For sunscreen use:

- apply liberally 15 minutes before sun exposure
- reapply at least every 2 hours
- use a water resistant sunscreen if swimming or sweating
  - Sun Protection Measures. Spending time in the sun increases your risk of skin cancer and early skin aging. To decrease this risk, regularly use a sunscreen with a Broad Spectrum SPF value of 15 or higher and other sun protection measures including:

- limit time in the sun, especially from 10 a.m. - 2p.m.

-wear long-sleeved shirts, pants, hats and sunglasses

- children under 6 months of age: Ask a doctor

OTHER INFORMATION

- protect the product in this container from excessive heat and direct sun

INACTIVE INGREDIENT

Inactive ingredientsWater,Cyclopentasiloxane,Isododecane,Isononyl Isononanoate,Glycerin,Cetyl PEF/PPG-10/1 Dimethicone, Dimethicone, Magnesium Sulfate,Polyglyceryl-4 Isostearate, Dimethicone/PEG-10/15 Crosspolymer,Disodium Stearoyl Glutamate,Disteardimonium Hectorite, Phenoxyethanol, Polybutene, Methylparaben, Alcohol Denat, Chlorphenesin, Acrylonitrile/methyl methacrylate/vinylidene chloride, Copolymer, Butylparaben, Aluminum Hydroxide, Sodium Hyaluronate, Isobutane,Dipropylene Glycol, Sodium Citrate, Tocopherol, Pentaerythrityl tetra-di-butyl hydroxyhydrocinnamate; may contain, Titanium Dioxide,Iron Oxides.

QUESTIONS or COMMENTS

1-8771-877-900-6700 Monday - Friday (9 a.m. - 5 p.m. EST)

Primary Package(Inner)

Outer Package (Secondary)

Shade Label